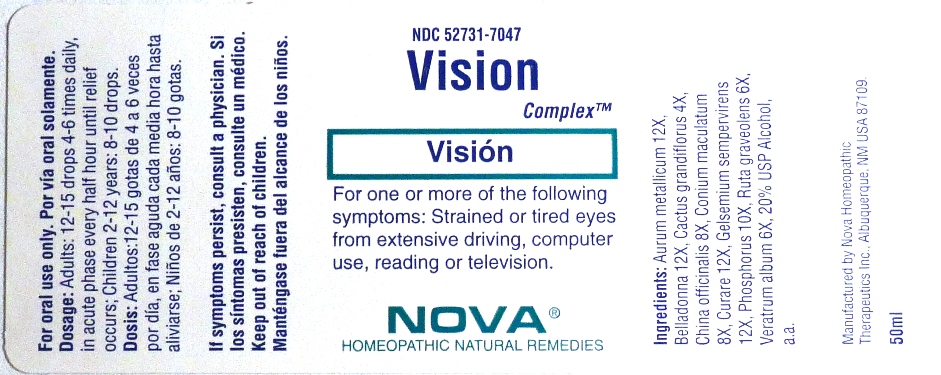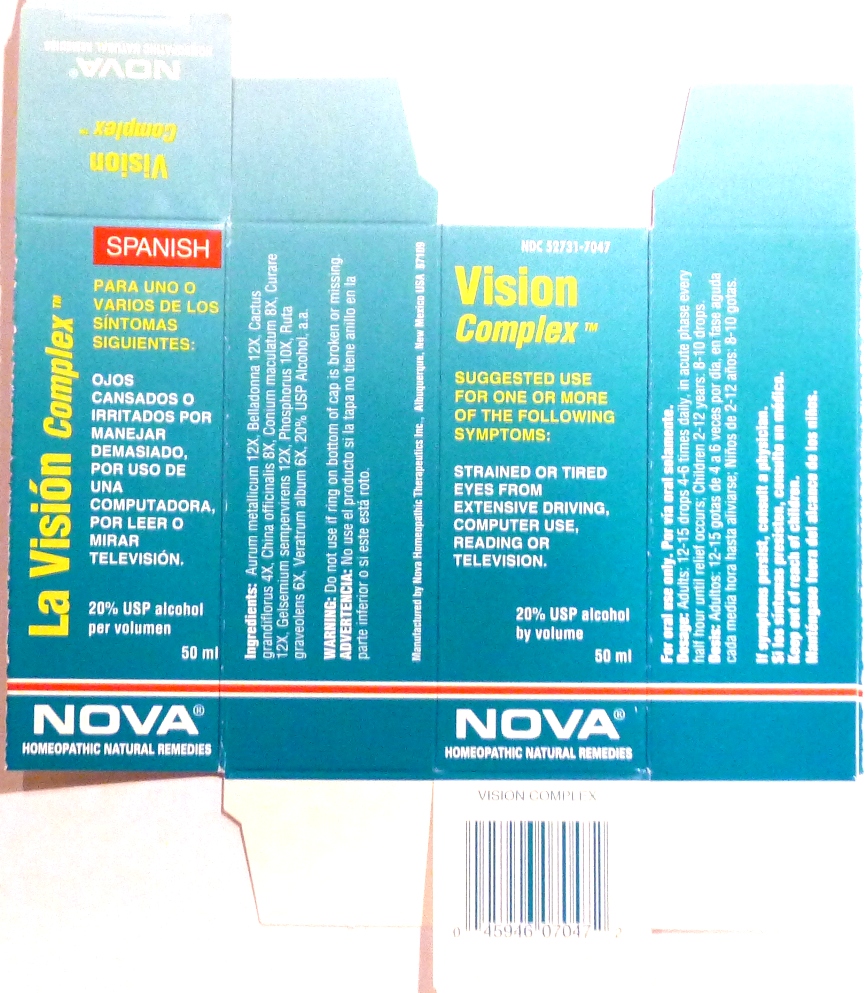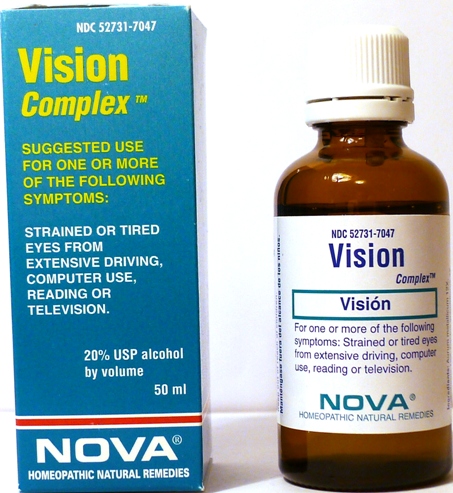 DRUG LABEL: Vision Complex
NDC: 52731-7047 | Form: LIQUID
Manufacturer: Nova Homeopathic Therapeutics, Inc.
Category: homeopathic | Type: HUMAN OTC DRUG LABEL
Date: 20110601

ACTIVE INGREDIENTS: GOLD 12 [hp_X]/1 mL; ATROPA BELLADONNA 12 [hp_X]/1 mL; SELENICEREUS GRANDIFLORUS STEM 4 [hp_X]/1 mL; CINCHONA PUBESCENS BARK 8 [hp_X]/1 mL; CONIUM MACULATUM FLOWERING TOP 8 [hp_X]/1 mL; TUBOCURARINE CHLORIDE 12 [hp_X]/1 mL; GELSEMIUM SEMPERVIRENS ROOT 12 [hp_X]/1 mL; PHOSPHORUS 10 [hp_X]/1 mL; RUTA GRAVEOLENS FLOWERING TOP 6 [hp_C]/1 mL; VERATRUM ALBUM ROOT 6 [hp_X]/1 mL
INACTIVE INGREDIENTS: ALCOHOL

Vision Complex

Purpose:

Suggested use for one or more of the following symptoms:
Strained or tired eyes from extensive driving, computer use, reading or television.

Usage and Dosage:

For oral use only.

DOSAGE AND ADMINISTRATION

Adults:
In Acute Phase:
12-15 drops, every half hour until relief occurs
When Relief Occurs:
12-15 drops, 4-6 times per day
Children 2-12 years:
8-10 drops, 4-6 times per day

Warnings:

Keep out of reach of children.

WARNINGS

If symptoms persist, consult a physician.
Do not use if ring on bottom of cap is broken or missing.

Active Ingredients:

Aurum metallicum 12X, Belladonna 12X, Cactus grandiflorus 4X, China officinalis 8X, Conium maculatum 8X, Curare 12X, Gelsemium sempervirens 12X, Phosphorus 10X, Ruta graveolens 6X, Veratrum album 6X

Inactive Ingredients:

Alcohol, 20% USP

QUESTIONS

Manufactured by Nova Homeopathic Therapeutics Inc., Albuquerque, New Mexico USA 87109
1-800-225-8094

PACKAGE LABEL

Vision Complex Product

Vision Complex Bottle Label

Vision Complex Box